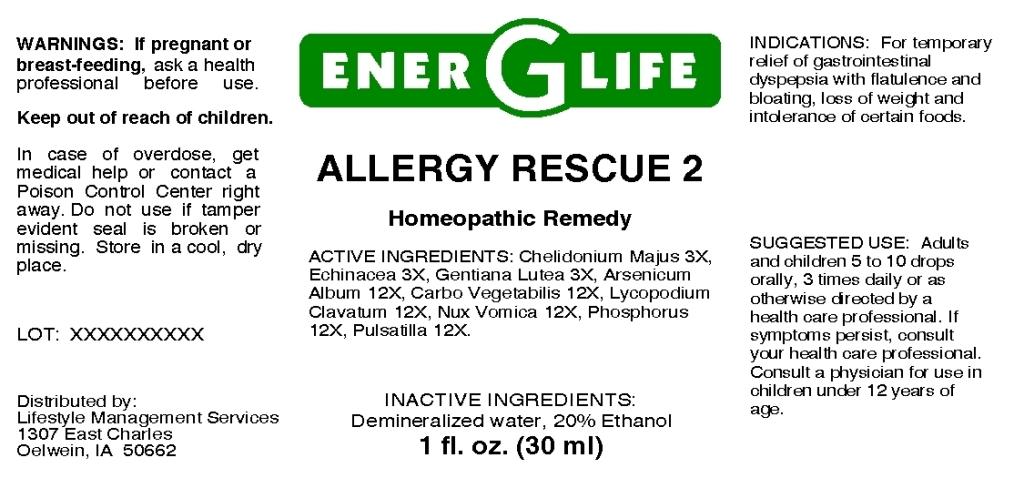 DRUG LABEL: Allergy Rescue
NDC: 57520-0652 | Form: LIQUID
Manufacturer: Apotheca Company
Category: homeopathic | Type: HUMAN OTC DRUG LABEL
Date: 20110330

ACTIVE INGREDIENTS: CHELIDONIUM MAJUS 3 [hp_X]/1 mL; ECHINACEA 3 [hp_X]/1 mL; GENTIANA LUTEA ROOT 3 [hp_X]/1 mL; ARSENIC TRIOXIDE 12 [hp_X]/1 mL; ACTIVATED CHARCOAL 12 [hp_X]/1 mL; LYCOPODIUM CLAVATUM SPORE 12 [hp_X]/1 mL; STRYCHNOS NUX-VOMICA SEED 12 [hp_X]/1 mL; PHOSPHORUS 12 [hp_X]/1 mL; PULSATILLA VULGARIS 12 [hp_X]/1 mL
INACTIVE INGREDIENTS: WATER; ALCOHOL

Allergy Rescue 2

ACTIVE INGREDIENT

ACTIVE INGREDIENTS: Chelidonium majus 3X, Echinacea 3X, Gentiana lutea 3X, Arsenicum album 12X, Carbo vegetabilis 12X, Lycopodium clavatum 12X, Nux vomica 12X, Phosphorus 12X, Pulsatilla 12X.

PURPOSE

INDICATIONS: For temporary relief of gastrointestinal dyspepsia with flatulence and bloating, loss of weight and intolerance of certain foods.

WARNINGS

WARNINGS: If pregnant or breast-feeding, ask a health professional before use.

Keep out of reach of children. In case of overdose, get medical help or contact a Poison Control Center right away.

Do not use if tamper evident seal is broken or missing. Store in a cool, dry place.

DOSAGE AND ADMINISTRATION

SUGGESTED USE: Adults and children 5 to 10 drops orally, 3 times daily or as otherwise directed by a health care professional. If symptoms persist, consult your health care professional. Consult a physician for use in children under 12 years of age.

INACTIVE INGREDIENTS: Demineralized water, 20% Ethanol.

KEEP OUT OF REACH OF CHILDREN. In case of overdose, get medical help or contact a Poison Control Center right away.

INDICATIONS AND USAGE

INDICATIONS: For temporary relief of gastrointestinal dyspepsia with flatulence and bloating, loss of weight and intolerance of certain foods.

QUESTIONS

Distributed by:

Lifestyle Management Services

1307 East Charles

Oelwein, IA 50662

PACKAGE LABEL

ENER G LIFE

ALLERGY RESCUE 2

Homeopathic Remedy

1 fl. oz. (30 ml)